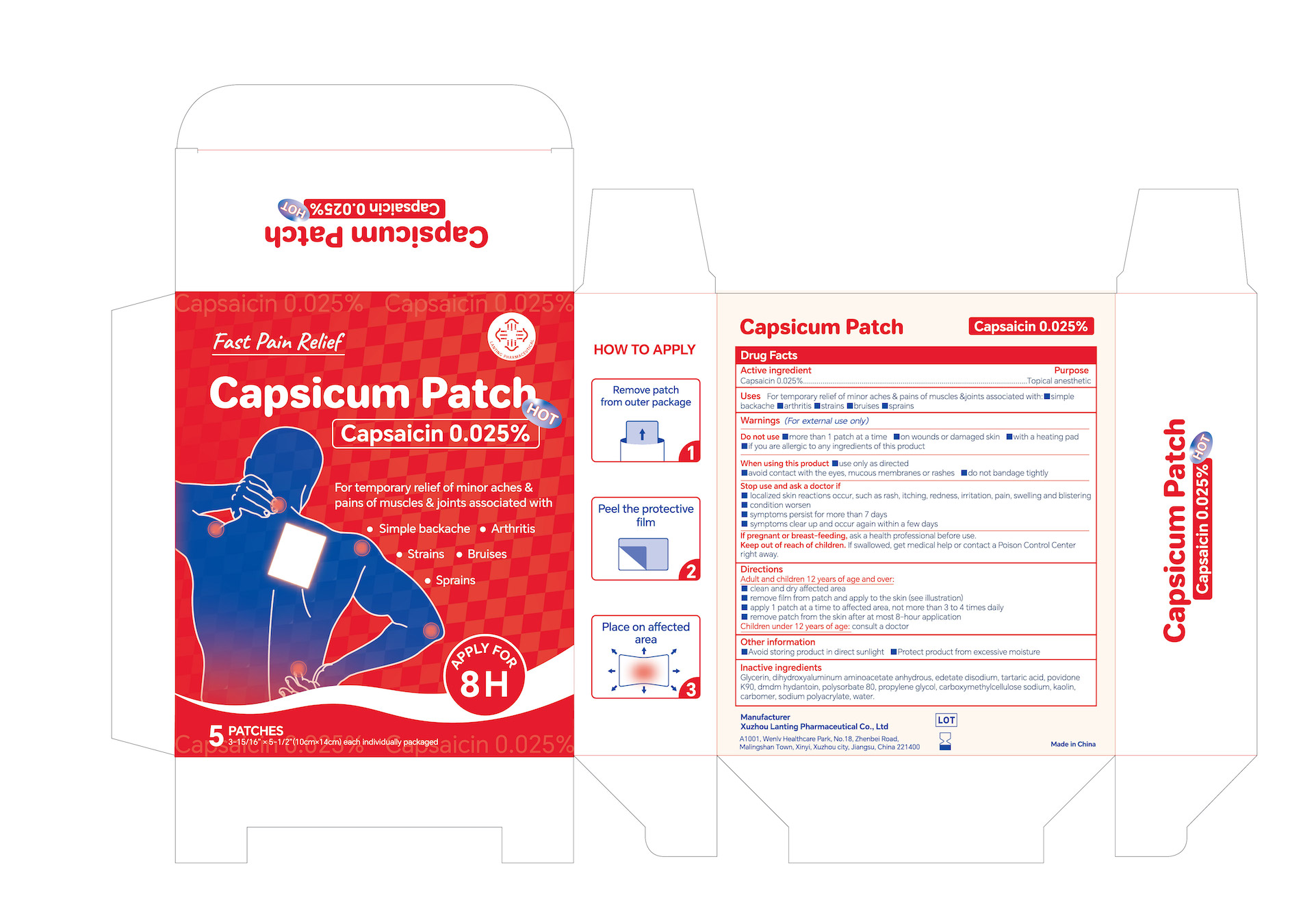 DRUG LABEL: 0.025% Capsaicin Pain relief Patch
NDC: 85323-001 | Form: PATCH
Manufacturer: Xuzhou Lanting Pharmaceutical Co., Ltd
Category: otc | Type: HUMAN OTC DRUG LABEL
Date: 20250301

ACTIVE INGREDIENTS: CAPSAICIN 0.025 g/100 g
INACTIVE INGREDIENTS: KAOLIN; CARBOMER; EDETATE DISODIUM; PROPYLENE GLYCOL; POLYSORBATE 80; SODIUM POLYACRYLATE (2500000 MW); GLYCERIN; DMDM HYDANTOIN; DIHYDROXYALUMINUM AMINOACETATE ANHYDROUS; WATER; TARTARIC ACID; POVIDONE K90; CARBOXYMETHYLCELLULOSE SODIUM

0.025% Capsaicin Pain relief Patch, Package NDC Code: 85323-001-00

Active Ingredient

Active Ingredient: 0.025% Capsaicin

Purpose

Purpose: Topical anesthetic

Warnings

Warnings (For external use only)

- Do not use
- more than 1 patch at a time
- on wounds or damaged skin
- with a heating pad
- if you are allergic to any ingredients of this product

When using this product

- use only as directed
- avoid contact with the eyes, mucous membranes or rashes
- do not bandage tightly

Stop use and ask a doctor if

- localized skin reactions occur, such as rash, itching, redness, irritation, pain, swelling and blistering
- condition worsen
- symptoms persist for more than 7 days
- symptoms clear up and occur again within a few days

If pregnant or breast-feeding, ask a health professional before use.

Keep out of reach of children. If swallowed, get medical help or contact a Poison Control Center right away.

Uses

Uses For temporary relief of minor aches & pains of muscles & joints associated with:

- simple backache
- arthritis
- strains
- bruises
- sprains

Other information

- Avoid storing product in direct sunlight
- Protect product from excessive moisture

Inactive Ingredients

Glycerin, dihydroxyaluminum aminoacetate anhydrous, edetate disodium, tartaric acid, povidone K90, dmdm hydantoin, polysorbate 80, propylene glycol, carboxymethylcellulose sodium, kaolin, carbomer, sodium polyacrylate, water.

Keep out of reach of children. If swallowed, get medical help or contact a Poison Control Center right away.

Directions

Uses For temporary relief of minor aches & pains of muscles & joints associated with:

- simple backache
- arthritis
- strains
- bruises
- sprains

Adult and children 12 years of age and over:
clean and dry affected area
remove film from patch and apply to the skin (see illustration)
apply 1 patch at a time to affected area, not more than 3 to 4 times daily
remove patch from the skin after at most 8-hour apolication
Children under 12 years of age: consult a doctor

DOSAGE AND ADMINISTRATION

Adult and children 12 years of age and over:
clean and dry affected area
remove film from patch and apply to the skin (see illustration)
apply 1 patch at a time to affected area, not more than 3 to 4 times daily
remove patch from the skin after at most 8-hour application

Children under 12 years of age: consult a doctor